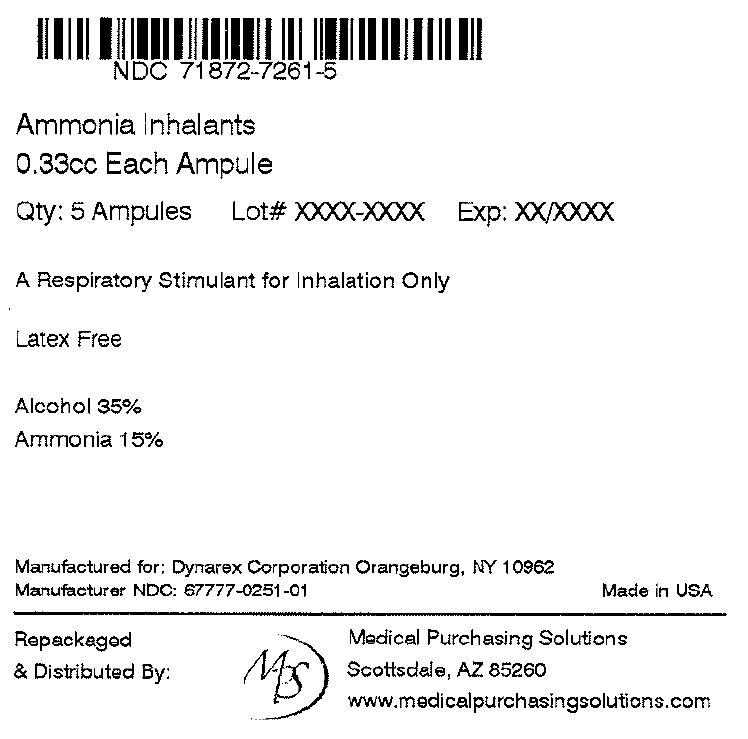 DRUG LABEL: Ammonia Inhalants
NDC: 71872-7261 | Form: INHALANT
Manufacturer: Medical Purchasing Solutions, LLC
Category: otc | Type: HUMAN OTC DRUG LABEL
Date: 20230427

ACTIVE INGREDIENTS: AMMONIA 0.05 g/0.33 mL
INACTIVE INGREDIENTS: ALCOHOL

1401 Ammonia Inhalants (Ampule) NDC 67777-251-01

active ingredient each inhalant purpose ammonia 15% inhalant

PURPOSE

Uses to prevent or treating fainting

warnings for external use only

do not use if you have breathing problems such as asthma or emphysema

stop use and ask a doctor if condition persists

KEEP OUT OF REACH OF CHILDREN

If swallowed get medical help or contact a Poison Control Center right away

DOSAGE AND ADMINISTRATION

Hold inhalant away from face and crush between thumb and forefinger. carefully approach crushed inhalant to nostrils of affected person.

STORAGE AND HANDLING

Store at room temperature away from light

INACTIVE INGREDIENT

alcohol fdc red dye 40 lavender oil, lemon oil, nutmeg oil, purified water usp

INDICATIONS AND USAGE

to prevent or treat fainting

WARNINGS

for external use only

PRINCIPAL DISPLAY PANEL

NDC 71872-7261-01

5 X 0.33cc Ampules

Ammonia inhalants

A respiratory stimulant for inhalation only latex free

Latex Free

Alcohol 35%

Ammonia 15%